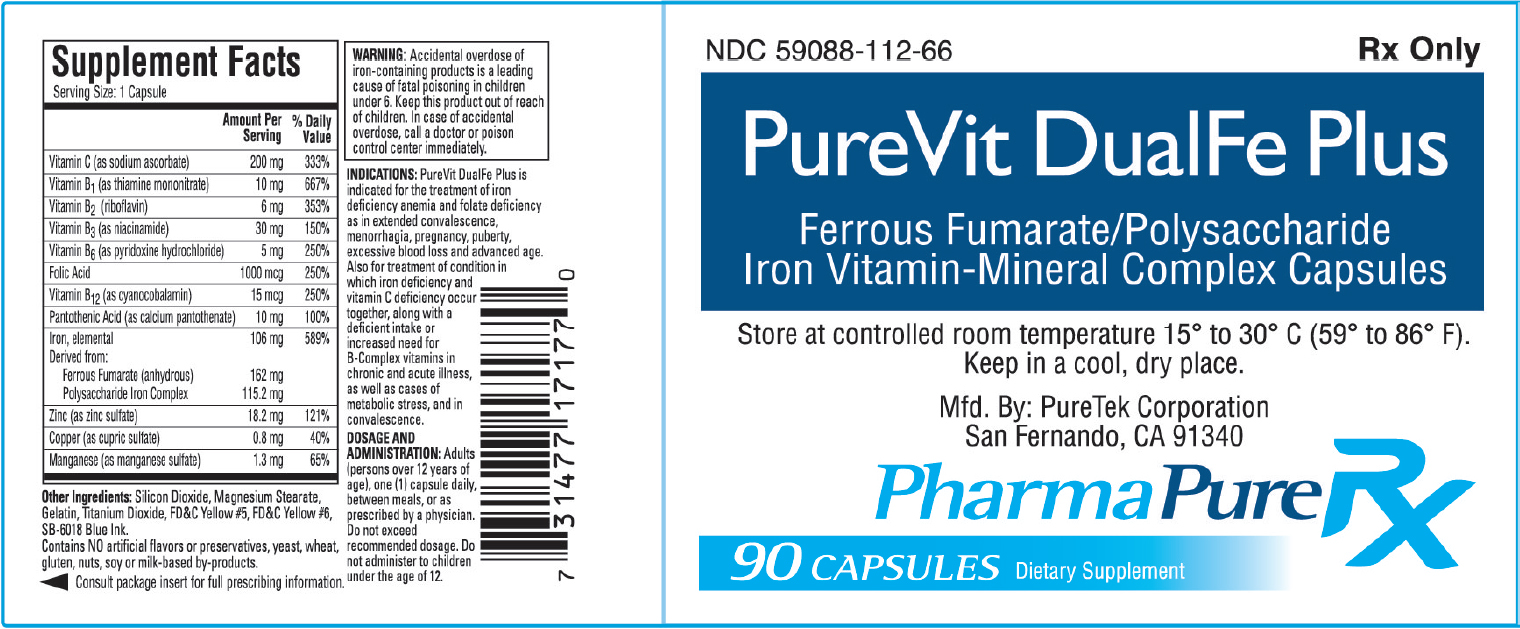 DRUG LABEL: PureVit DualFe Plus
NDC: 59088-112 | Form: CAPSULE
Manufacturer: PureTek Corporation
Category: prescription | Type: HUMAN PRESCRIPTION DRUG LABEL
Date: 20230111

ACTIVE INGREDIENTS: CUPRIC SULFATE 0.8 mg/1 1; FERROUS FUMARATE 53 mg/1 1; IRON DEXTRAN 53 mg/1 1; RIBOFLAVIN 6 mg/1 1; NIACINAMIDE 30 mg/1 1; PYRIDOXINE HYDROCHLORIDE 5 mg/1 1; FOLIC ACID 1 mg/1 1; CYANOCOBALAMIN 15 ug/1 1; CALCIUM PANTOTHENATE 10 mg/1 1; SODIUM ASCORBATE 200 mg/1 1; THIAMINE MONONITRATE 10 mg/1 1; ZINC SULFATE 18.2 mg/1 1; MANGANESE SULFATE 1.3 mg/1 1
INACTIVE INGREDIENTS: SILICON DIOXIDE; MAGNESIUM STEARATE; GELATIN; TITANIUM DIOXIDE; FD&C YELLOW NO. 5; FD&C YELLOW NO. 6

PureVit DualFe Plus

CLINICAL PHARMACOLOGY:

PureVit DualFe Plus is unique in that it utilizes two different forms of iron, i.e., Ferrous Fumarate and Polysaccharide Iron Complex (as cell-contracted akaganeite), making available a total of 106 mg of elemental iron per capsule as follows:

Ferrous Fumarate (anhydrous) 162 mg
Polysaccharide Iron Complex (PIC) 115.2 mg
Subclinical B-Group vitamin deficiencies have greatly increased in recent years due to changes in dietetic habits, increase in the use of sugar, and the excessive milling of flour and cereals. With thiamine deficiencies so prevalent in a healthy populace, it is self-evident that the unwell person is particularly prone to thiamine avitaminosis. This is true of the anemic individual with his or her poor appetite and disturbed digestive functions. Folic acid is best known for its role in megaloblastic anemias. Zinc has been recognized in the nutrition of animals and humans, even though the evidence for an uncomplicated zinc deficiency in humans is limited.

Ferrous Fumarate: Provides about 53 mg of elemental iron per dose. Ferrous Fumarate is an anhydrous salt of a combination of ferrous iron and fumaric acid, containing 33% of iron per weight. The acute toxicity in experimental animals is low and Ferrous Fumarate is well tolerated clinically. As a ferrous salt, it is more efficiently absorbed in the duodenum. Ferrous Fumarate contrasts very favorably with the availability of the 20% of elemental iron of ferrous sulfate, and the 13% of elemental iron of ferrous gluconate.

Polysaccharide Iron Complex: Provides about 53 mg of elemental iron, as a cell-contracted akaganeite. It is a product of ferric iron complexed to a low molecular weight polysaccharide. This polysaccharide is produced by extensive hydrolysis of starch and is a dark brown powder that dissolves in water to form a very dark brown solution, which is virtually odorless and tasteless.

Folic Acid:

Folic Acid is one of the most important hematopoetic agents necessary for proper regeneration of the blood-forming elements and their function. Folic acid is a precursor to a large family of compounds which serve as coenzymes in carbon transfer reactions. These reactions are required for the synthesis of purine and pyrimidine bases, inter-conversion of glycine and serine, biosynthesis of methionine methyl groups and degradation of histidine. Additionally, folic acid increases jejunal glycolytic enzymes and is involved in the desaturation and hydroxylation of long-chain fatty acids in the brain. A deficiency in folic acid results in megaloblastic anemia.

INDICATIONS:

PureVit DualFe Plus is indicated for the treatment of iron deficiency anemia and folate deficiency as in extended convalescence, menorrhagia, pregnancy, puberty, excessive blood loss and advanced age. Also for treatment of condition in which iron deficiency and vitamin C deficiency occur together, along with a deficient intake or increased need for B-Complex vitamins in chronic and acute illness, as well as cases of metabolic stress, and in convalescence.

CONTRAINDICATIONS:

PureVit DualFe Plus is contraindicated in patients with known hypersensitivity to any of its ingredients; also, all iron compounds are contraindicated in patients with hemosiderosis, hemochromatosis, or hemolytic anemias. Pernicious anemia is a contraindication, as folic acid may obscure its signs and symptoms.

WARNING:

Accidental overdose of Iron-containing products is the leading cause of fatal poisoning of children under 6. Keep this product out of reach of children. In case of accidental overdose, call a doctor or Poison Control Center immediately.

Folic acid alone is improper therapy in the treatment for pernicious anemia and other megaloblastic anemias where Vitamin B12 is deficient.

PRECAUTIONS:

General: Folic Acid in doses above 0.1 mg - 0.4 mg daily may obscure pernicious anemia, in that hematological remission can occur while neurological manifestations, remain progressive.

Pediatric Use:

Safety and effectiveness in pediatric patients have not been established.

Geriatric Use:

No clinical studies have been performed in patients age 65 and over to determine whether older patients respond differently from younger patients. Dosage should always begin at the low end of the dosage scale and should consider that elderly patients may have decreased hepatic, renal or cardiac function, and of concomitant diseases.

Adverse Reactions:

Folic Acid: Allergic sensitizations have been reported following both oral and parenteral administration of folic acid.

Ferrous Fumarate: Gastrointestinal disturbances (anorexia, nausea, diarrhea, constipation) occur occasionally, but are usually mild and may subside with continuation of therapy. Although the absorption of iron is best when taken between meals, giving PureVit DualFe Plus after meals may control occasional gastrointestinal disturbances. PureVit DualFe Plus is best absorbed when taken at bedtime.

Call your doctor for medical advice about side effects. You may report suspected side effects to the FDA at 1-800-FDA-1088.

OVERDOSE:

Iron: Signs and Symptoms: Iron is toxic. Acute overdosage of iron may cause nausea and vomiting and, in severe cases, cardiovascular collapse and death. Other symptoms include pallor and cyanosis, melena, shock, drowsiness and coma. The estimated overdose of orally ingested iron is 300 mg/kg body weight. When overdoses are ingested by children, severe reactions, including fatalities, have resulted. PureVit DualFe Plus should be stored beyond the reach of children to prevent against accidental iron poisoning. Keep this and all other drugs out of reach of children.

Treatment: For specific therapy, exchange transfusion and chelating agents should be used. For general management, perform gastric lavage with sodium bicarbonate solution or milk. Administer intravenous fluids and electrolytes and use oxygen.

DOSAGE AND ADMINISTRATION:

Adults (persons over 12 years of age), one (1) capsule daily, between meals, or as prescribed by a physician. Do not exceed recommended dosage. Do not administer to children under the age of 12.

HOW SUPPLIED:

PureVit DualFe Plus are yellow capsules imprinted horizontally "P-112", bottles of 90 capsules NDC 59088-112-66. Dispense in a tight, light-resistant container as defined in the USP/NF with a child resistant closure.

Store at 20° to 25°C (68° to 77°F). [See USP Controlled Room Temperature]. Keep in a cool, dry place.